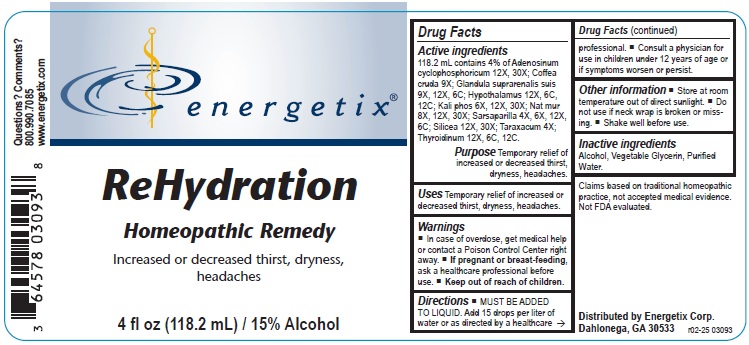 DRUG LABEL: ReHydration
NDC: 64578-0175 | Form: LIQUID
Manufacturer: Energetix Corporation
Category: homeopathic | Type: HUMAN OTC DRUG LABEL
Date: 20251217

ACTIVE INGREDIENTS: ADENOSINE CYCLIC PHOSPHATE 12 [hp_X]/118.2 mL; ARABICA COFFEE BEAN 9 [hp_X]/118.2 mL; SUS SCROFA ADRENAL GLAND 9 [hp_X]/118.2 mL; BOS TAURUS HYPOTHALAMUS 12 [hp_X]/118.2 mL; DIBASIC POTASSIUM PHOSPHATE 6 [hp_X]/118.2 mL; SODIUM CHLORIDE 8 [hp_X]/118.2 mL; SARSAPARILLA 4 [hp_X]/118.2 mL; SILICON DIOXIDE 12 [hp_X]/118.2 mL; TARAXACUM OFFICINALE ROOT 4 [hp_X]/118.2 mL; THYROID, UNSPECIFIED 12 [hp_X]/118.2 mL
INACTIVE INGREDIENTS: ALCOHOL; GLYCERIN; WATER

ReHydration

ACTIVE INGREDIENT

Active ingredients 118.2 mL contains 4% of Adenosinum cyclophosphoricum 12X, 30X; Coffea cruda 9X; Glandula suprarenalis suis 9X, 12X, 6C; Hypothalamus 12X, 6C, 12C; Kali phos 6X, 12X, 30X; Nat mur 8X, 12X, 30X; Sarsaparilla 4X, 6X, 12X, 6C; Silicea 12X, 30X; Taraxacum 4X; Throidnium 12X, 6C, 12C.

Claims based on traditional homeopathic practice, not accepted medical evidence. Not FDA evaluated.

INDICATIONS AND USAGE

Uses Temporary relief of increased or decreased thirst, dryness, headaches.

Warnings

• In case of overdose, get medical help or contact a Poison Control Center right away.

• If pregnant or breast-feeding, ask a healthcare professional before use.

• Keep out of reach of children.

Directions

• MUST BE ADDED TO LIQUID. Add 15 drops per liter of water or as directed by a healthcare professional. Shake well before use.

• Consult a physician for use in children under 12 years of age or if symptoms worsen or persist.

Other information

• Store at room temperature out of direct sunlight.

• Do not use if neck wrap is broken or missing.

• Shake well before use.

Inactive ingredients Alcohol, Vegetable Glycerin, Purified Water.

QUESTIONS

Distributed by

Energetix Corp.

Dahlonega, GA 30533

Questions? Comments?

800.990.7085

www.energetix.com

PACKAGE LABEL

energetix

ReHydration

Homepathic Remedy

Increased or decreased thirst, dyness, headaches

4 fl oz (118.2 mL) / 15% Alcohol

PURPOSE

Purpose Temporary relief of increased or decreased thirst, dryness, headaches.